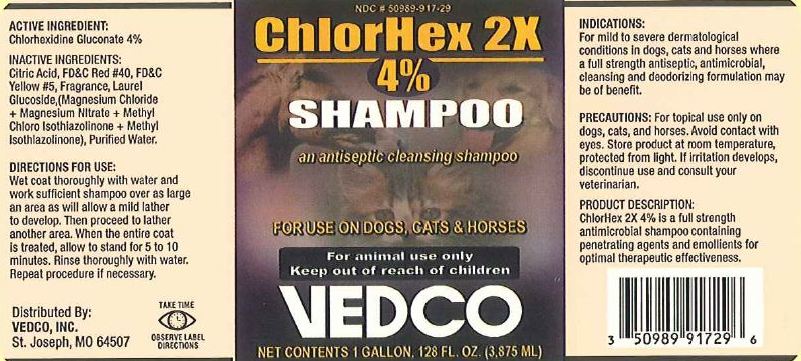 DRUG LABEL: ChlorHex 2X
NDC: 50989-917 | Form: SHAMPOO
Manufacturer: Vedco, Inc
Category: animal | Type: OTC ANIMAL DRUG LABEL
Date: 20120221

ACTIVE INGREDIENTS: CHLORHEXIDINE GLUCONATE 40.000 g/1.0 L

Chlorhex 2x Shampoo

Active Ingredient:

Chlorhexidine Gluconate 4%

Purpose:

An antiseptic cleansing shampoo

Use:

On dogs, cats & horses

Warnings:

Avoid contact with eyes

Precautions:

For topical use only on dogs, cats and horses. If irritation develops, discontinue use and consult your veterinarian.

Keep out of reach of children

Directions for Use:

Wet coat thoroughly with water and work sufficient shampoo over as large an area as will allow a mild lather to develop. Then proceed to lather another area. When the entire coat is treated, allow to stand 5 to 10 minutes. Rinse thoroughly with water. Repeat procedure if necessary.

For animal use only

Storage:

Store product at room temperature, protected from light.

Indications:

For mild to severe dermatological conditions where a full strength antiseptic, antimicrobial, cleansing and deoderizing formulation may be of benefit.

Inactive Ingredients:

Citric Acid, FD&C Red #40, FD&C Yellow #5, Fragrance, Laurel Glucoside, (Magnesium Chloride + Magnesium Nitrate + Methyl Chloro Isothiazolinone + Methyl Isothiazolinone), Purified Water

Package Label:

ChlorHex 2X Shampoo 128oz